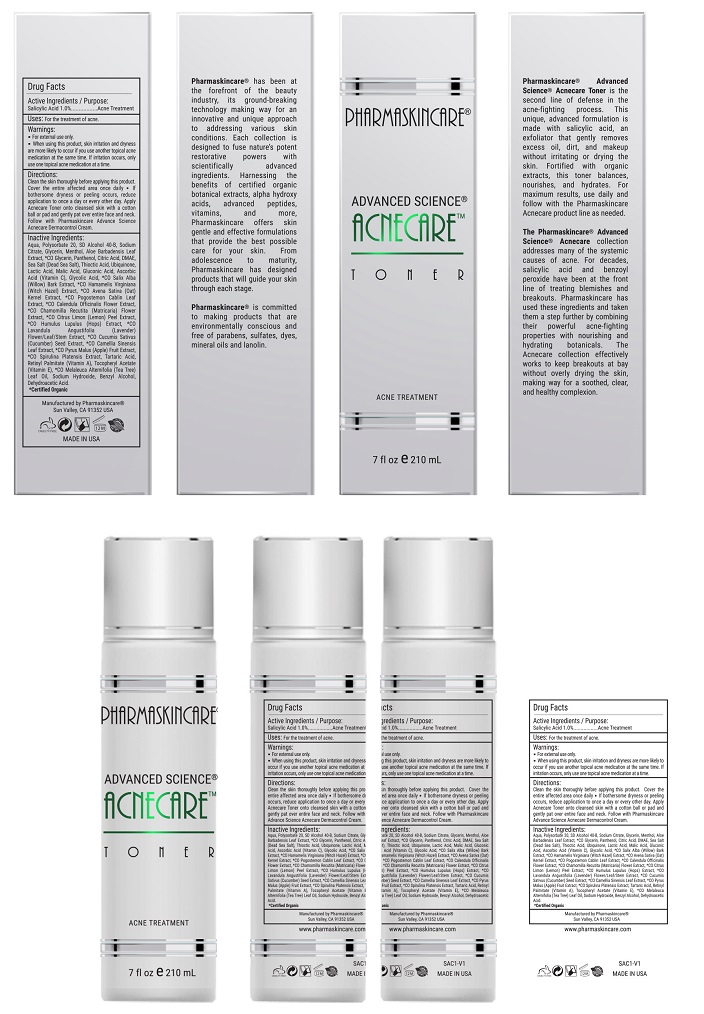 DRUG LABEL: Pharmaskincare Acnecare Toner
NDC: 68062-9111 | Form: SOLUTION
Manufacturer: Spa de Soleil
Category: otc | Type: HUMAN OTC DRUG LABEL
Date: 20171011

ACTIVE INGREDIENTS: SALICYLIC ACID 0.013 mg/2.5 mL
INACTIVE INGREDIENTS: ALCOHOL; SODIUM CITRATE; WATER; GLYCERIN; POLYSORBATE 20; MENTHOL

Pharmaskincare Acnecare Toner

Active Ingredient

Salicylic Acid 1.0%

Purpose

Acne Treatment

Warnings

- For external use only.
- When using this product : skin irritation and dryness is more likely to occur if you use another topical acne medication at the same time. If irritation occurs, only use one topical acne medication at a time.

Directions

Clean the skin thoroughly before applying this product. Cover the entire affected area with a thin layer and rinse thoroughly one to three times daily. Because excessive drying of the skin may occur, start with one application daily, then gradually increase to two or three times daily if needed or as directed by a doctor.

Massage Acnecare Toner onto cleansed, damp skin with a cotton ball or pad and gently pat over entire face and neck. Follow with Pharmaskincare Acnecare Dermacontrol Cream.

Uses:

For the treatment of acne.

Inactive Ingredients:

Water, Polysorbate 20, SD Alcohol 40-B, Sodium Citrate, Glycerin, Menthol, Aloe Barbadensis Leaf Extract, *CO Glycerin, Panthenol, Citric Acid, Sea Salt (Dead Sea Salt), DMAE, Thioctic Acid, Ubiquinone, Lactic Acid, Malic Acid, Malus Domestica Fruit Cell Culture Extract, Gluconic Acid, Ascorbic Acid (Vitamin C), Glycolic Acid, *CO Salix Alba (Willow) Bark Extract, *CO Hamamelis Virginiana (Witch Hazel) Extract, *CO Avena Sativa (Oat) Kernel Extract, *CO Pogostemon Cablin Leaf Extract, *CO Calendula Officinalis Flower Extract, *CO Chamomilla Recutita (Matricaria) Flower Extract, *CO Citrus Limon (Lemon) Peel Extract, *CO Humulus Lupulus (Hops) Extract, *CO Lavandula Angustifolia (Lavender) Flower/Leaf/Stem Extract, *CO Cucumis Sativus (Cucumber) Seed Extract, *CO Camellia Sinensis Leaf Extract, *CO Pyrus Malus (Apple) Fruit Extract, *CO Spirulina Platensis Extract, Xanthan Gum, Tartaric Acid, Lecithin, Retinyl Palmitate (Vitamin A), Tocopheryl Acetate (Vitamin E), *CO Melaleuca Alternifolia (Tea Tree) Leaf Oil, Sodium Hydroxide, Benzyl Alcohol, Dehydroacetic Acid

Warning

Keep out of reach of children.

PACKAGE LABEL

Pharmaskincare AcnecareToner.jpg